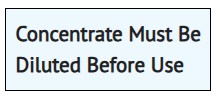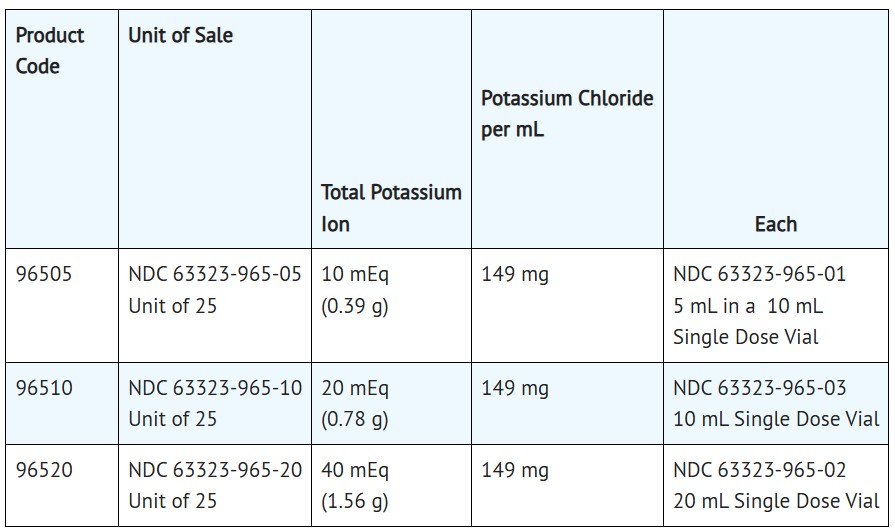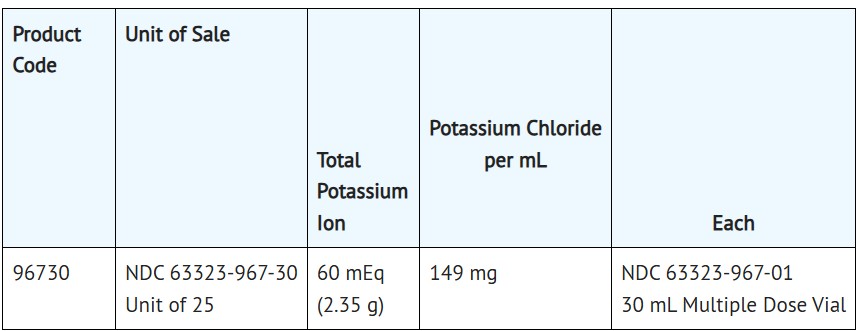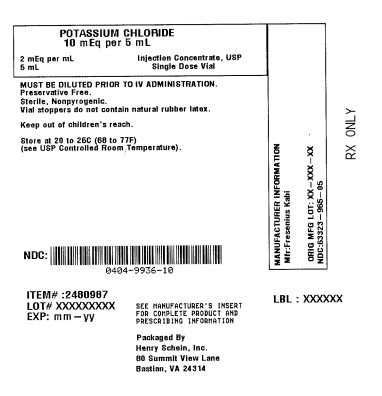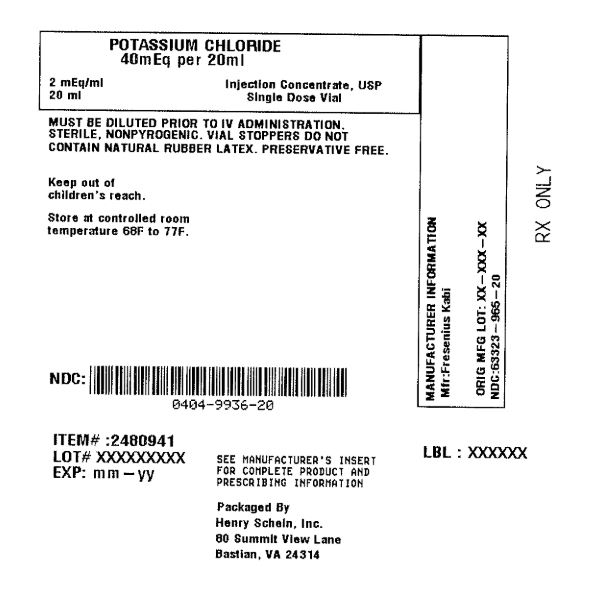 DRUG LABEL: Potassium Chloride
NDC: 0404-9936 | Form: INJECTION, SOLUTION, CONCENTRATE
Manufacturer: Henry Schein, Inc.
Category: prescription | Type: HUMAN PRESCRIPTION DRUG LABEL
Date: 20250812

ACTIVE INGREDIENTS: POTASSIUM CHLORIDE 2 meq/1 mL
INACTIVE INGREDIENTS: POTASSIUM HYDROXIDE

POTASSIUM CHLORIDE
FOR INJECTION CONCENTRATE, USP

Rx Only

FOR INTRAVENOUS INFUSION ONLY

MUST BE DILUTED PRIOR TO INJECTION

Description

Potassium Chloride for Injection Concentrate, USP is a sterile, nonpyrogenic concentrated solution of Potassium Chloride, USP in Water for Injection to be administered by intravenous infusion only after dilution in a larger volume of fluid.

Each mL of Potassium Chloride for Injection Concentrate contains 2 mEq of K^+ and Cl^– equivalent to 149 mg of potassium chloride and has an osmolarity of 4000 mOsmol/L (calc). A more concentrated Potassium Chloride for Injection Concentrate is also available. Each mL of this injection contains 3 mEq of K^+ and Cl^– equivalent to 224 mg of potassium chloride and has an osmolarity of 6000 mOsmol/L(calc).

pH (4.0-8.0) may have been adjusted with hydrochloric acid and if necessary, potassium hydroxide.

Some packages are intended for multiple dose use and contain preservatives (0.05% methylparaben and 0.005% propylparaben). A summary of the available products is presented in the HOW SUPPLIED section.

Potassium Chloride for Injection Concentrate (appropriately diluted) is a parenteral fluid and electrolyte replenisher.

Clinical Pharmacology

Potassium is the chief cation of body cells (160 mEq/L of intracellular water) and is concerned with the maintenance of body fluid composition and electrolyte balance. Potassium participates in carbohydrate utilization and protein synthesis, and is critical in the regulation of nerve conduction and muscle contraction, particularly in the heart. Chloride, the major extracellular anion, closely follows the metabolism of sodium, and changes in the acid-base balance of the body are reflected by changes in the chloride concentration.

Normally about 80 to 90% of the potassium intake is excreted in the urine, the remainder in the stools and to a small extent, in the perspiration. The kidney does not conserve potassium well, so that during fasting, or in patients on a potassium-free diet, potassium loss from the body continues resulting in potassium depletion. A deficiency of either potassium or chloride will lead to a deficit of the other.

Indications and Usage

Potassium Chloride for Injection Concentrate, USP is indicated in the treatment of potassium deficiency states when oral replacement is not feasible.

Contraindications

Potassium chloride for Injection Concentrate is contraindicated in diseases where high potassium levels may be encountered, and in patients with hyperkalemia, renal failure and in conditions in which potassium retention is present.

Warnings

Potentially Fatal Cardiac Adverse Reactions with Undiluted Intravenous Administration

Direct patient injection of potassium chloride at this concentration may be instantaneously fatal. Potassium Chloride for Injection Concentrate must be diluted before administration. Fatal cardiac arrhythmia and cardiac arrest have occurred when potassium chloride was administered in an undiluted form.

To avoid potassium intoxication, do not infuse these solutions rapidly. In patients with renal insufficiency, administration of potassium chloride may cause potassium intoxication and life-threatening hyperkalemia.

The administration of intravenous solutions can cause fluid and/or solute overload resulting in dilution of serum electrolyte concentrations, overhydration, congested states or pulmonary edema. The risk of dilutional states is inversely proportional to the electrolyte concentration. The risk of solute overload causing congested states with peripheral and pulmonary edema is directly proportional to the electrolyte concentration.

In patients with diminished renal function, administration of solutions containing potassium ions may result in potassium retention.

This product contains aluminum that may be toxic. Aluminum may reach toxic levels with prolonged parenteral administration if kidney function is impaired. Premature neonates are particularly at risk because their kidneys are immature, and they require large amounts of calcium and phosphate solutions, which contain aluminum. Research indicates that patients with impaired kidney function, including premature neonates, who receive parenteral levels of aluminum at greater than 4 to 5 mcg/kg/day accumulate aluminum at levels associated with central nervous system and bone toxicity. Tissue loading may occur at even lower rates of administration.

Precautions

General
Clinical evaluation and periodic laboratory determinations are necessary to monitor changes in fluid balance, electrolyte concentrations, and acid-base balance during prolonged parenteral therapy or whenever the condition of the patient warrants such evaluation. Significant deviations from normal concentrations may require the use of additional electrolyte supplements, or the use of electrolyte-free dextrose solutions to which individualized electrolyte supplements may be added.

Potassium therapy should be guided primarily by serial electrocardiograms, especially in patients receiving digitalis. Serum potassium levels are not necessarily indicative of tissue potassium levels. Solutions containing potassium should be used with caution in the presence of cardiac disease, particularly in the presence of renal disease, and in such instances, cardiac monitoring is recommended.

Solutions containing dextrose should be used with caution in patients with overt or known subclinical diabetes mellitus, or carbohydrate intolerance for any reason.

If the administration is controlled by a pumping device, care must be taken to discontinue pumping action before the container runs dry or air embolism may result.

Pregnancy
Teratogenic Effects: Pregnancy Category C- Animal reproduction studies have not been conducted with potassium chloride. It is also not known whether potassium chloride can cause fetal harm when administered to a pregnant woman or can affect reproduction capacity. Potassium chloride should be given to a pregnant woman only if clearly needed.

Adverse Reactions

To report SUSPECTED ADVERSE REACTIONS, contact Fresenius Kabi USA, LLC at 1-800-551-7176 or FDA at 1-800-FDA-1088 or www.fda.gov/medwatch.

Reactions which may occur because of the solution or the technique of administration include febrile response, infection at the site of injection, venous thrombosis or phlebitis extending from the site of injection, extravasation, hypervolemia, and hyperkalemia.

Too rapid infusion of hypertonic solutions may cause local pain and, rarely, vein irritation. Rate of administration should be adjusted according to tolerance.

Reactions reported with the use of potassium-containing solutions include nausea, vomiting, abdominal pain and diarrhea. The signs and symptoms of potassium intoxication include paresthesias of the extremities, areflexia, muscular or respiratory paralysis, mental confusion, weakness, hypotension, cardiac arrhythmias, heart block, electrocardiographic abnormalities and cardiac arrest. Potassium deficits result in disruption of neuromuscular function, and intestinal ileus and dilatation.

If an adverse reaction does occur, discontinue the infusion, evaluate the patient, institute appropriate therapeutic countermeasures and save the remainder of the fluid for examination if deemed necessary.

Overdosage

In the event of fluid overload during parenteral therapy, reevaluate the patient's condition, and institute appropriate corrective treatment.

In the even of overdosage with potassium-containing solutions, discontinue the infusion immediately and institute corrective therapy to reduce serum potassium levels.
Treatment of hyperkalemia includes the following:

1. Dextrose Injection, USP 10% or 25%, containing 10 units of crystalline insulin per 20 grams of dextrose administered intravenously, 300 to 500 mL/hour.
2. Absorption and exchange of potassium using sodium or ammonium cycle cation exchange resin, orally and as retention enema.
3. Hemodialysis and peritoneal dialysis. The use of potassium-containing foods or medications must be eliminated. However, in cases of digitalization, too rapid a lowering of plasma potassium concentration can cause digitalis toxicity.

Dosage and Administration

Potassium Chloride for Injection Concentrate must be diluted before administration. Care must be taken to ensure there is complete mixing of the potassium chloride with the large volume fluid, particularly if soft of bag type containers are used.

The dose and rate of administration are dependent upon the specific condition of each patient.

If the serum potassium level is greater than 2.5 mEq/L, potassium can be given at a rate not to exceed 10 mEq/hour and in a concentration of up to 40 mEq/L. The 24 hour total dose should not exceed 200 mEq.

If urgent treatment is indicated (serum potassium level less than 2mEq/L and electrocardiographic changes and/or muscle paralysis), potassium chloride may be infused very cautiously at a rate of up to 40 mEq/hour. In such cases, continuous cardiac monitoring is essential. As much as 400 mEq may be administered in a 24 hour period. In critical conditions, potassium chloride may be administered in saline (unless contraindicated) rather than in dextrose containing fluids, as a dextrose may lower serum potassium levels.

Prior to entering a vial, cleanse the rubber closure with a suitable antiseptic agent.

Parenteral drug products should be inspected visually for particulate matter and discoloration prior to administration whenever solution and container permit.

How Supplied

The following are packaged in plastic vials.

These are Single Dose Vials, no preservative added, packaged 25 vials per tray. Unused portion of vial should be discarded.

This is a Multiple Dose Vial, preserved with 0.05% methylparaben and 0.005% propylparaben, packaged 25 vials per tray.

Store at 20° to 25°C (68° to 77°F) [see USP Controlled Room Temperature].

Use only if solution is clear, seal intact and undamaged.

Vial stoppers do not contain natural rubber latex.

Product repackaged by: Henry Schein, Inc., Bastian, VA 24314
From Original Manufacturer/Distributor's NDC and Unit of Sale | To Henry Schein Repackaged Product NDC and Unit of Sale | Total Strength/Total Volume (Concentration) per unit
NDC 63323-965-05 Unit of 25 | NDC 0404-9936-10 1 5 mL in a 10 mL Single Dose Vial in a bag (Vial bears NDC 63323-965-01) | 10 mEq (0.39 g) 149 mg per mL
NDC 63323-965-20 Unit of 25 | NDC 0404-9936-20 1 20 mL Single Dose Vial in a bag (Vial bears NDC 63323-965-02) | 40 mEq (1.56 g) 149 mg per mL

FRESENIUS KABI

Lake Zurich, IL 60047
www.fresenius-kabi.com/us
45767H

Revised: February 2023